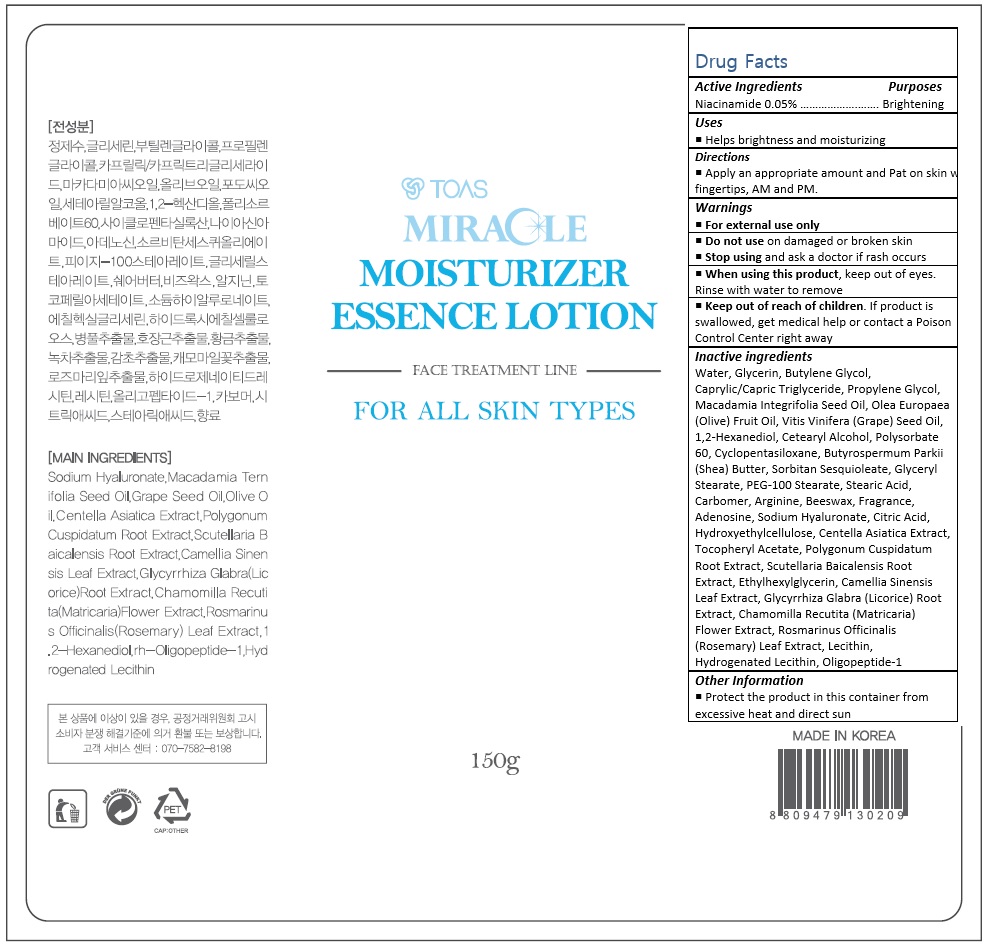 DRUG LABEL: Miracle Moisturizer Essence
NDC: 72557-002 | Form: LOTION
Manufacturer: TOAS Co., Ltd.
Category: otc | Type: HUMAN OTC DRUG LABEL
Date: 20180920

ACTIVE INGREDIENTS: NIACINAMIDE 0.075 g/150 g
INACTIVE INGREDIENTS: WATER; GLYCERIN; BUTYLENE GLYCOL; MEDIUM-CHAIN TRIGLYCERIDES; PROPYLENE GLYCOL; OLIVE OIL; GRAPE SEED OIL; 1,2-HEXANEDIOL; CETOSTEARYL ALCOHOL; POLYSORBATE 60; CYCLOMETHICONE 5

Drug Facts

ACTIVE INGREDIENT

Niacinamide 0.05%

PURPOSE

Brightening

INDICATIONS AND USAGE

Helps brightness and moisturizing

DOSAGE AND ADMINISTRATION

Apply an appropriate amount and Pat on skin with fingertips, AM and PM.

WARNINGS

For external use only.
Do not use on damaged or broken skin.
When using this product, keep out of eyes. Rinse with water to remove.
Stop using and ask a doctor if rash occurs.

KEEP OUT OF REACH OF CHILDREN

Keep out of reach of the children. If product is swallowed, get medical help or contact a poison control center right away.

INACTIVE INGREDIENT

Water, Glycerin, Butylene Glycol, Caprylic/Capric Triglyceride, Propylene Glycol, Macadamia Integrifolia Seed Oil, Olea Europaea (Olive) Fruit Oil, Vitis Vinifera (Grape) Seed Oil, 1,2-Hexanediol, Cetearyl Alcohol, Polysorbate 60, Cyclopentasiloxane, Butyrospermum Parkii (Shea) Butter, Sorbitan Sesquioleate, Glyceryl Stearate, PEG-100 Stearate, Stearic Acid, Carbomer, Arginine, Beeswax, Fragrance, Adenosine, Sodium Hyaluronate, Citric Acid, Hydroxyethylcellulose, Centella Asiatica Extract, Tocopheryl Acetate, Polygonum Cuspidatum Root Extract, Scutellaria Baicalensis Root Extract, Ethylhexylglycerin, Camellia Sinensis Leaf Extract, Glycyrrhiza Glabra (Licorice) Root Extract, Chamomilla Recutita (Matricaria) Flower Extract, Rosmarinus Officinalis (Rosemary) Leaf Extract, Lecithin, Hydrogenated Lecithin, Oligopeptide-1